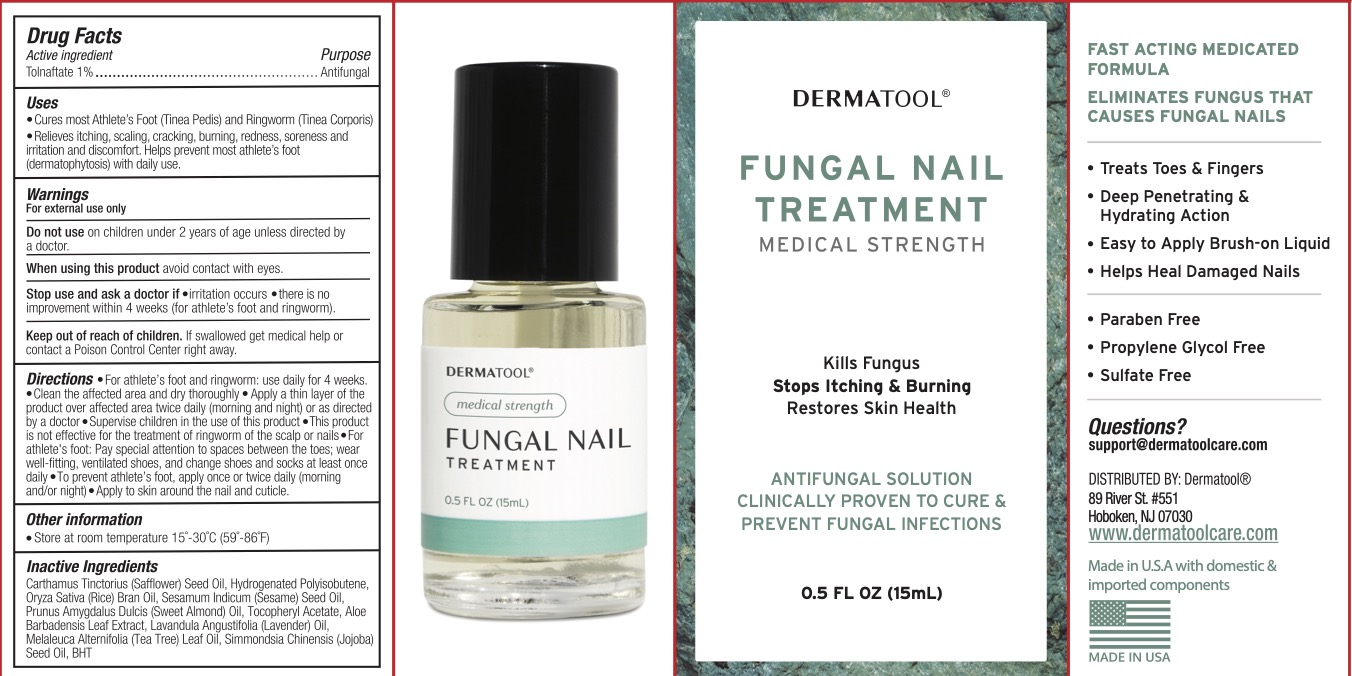 DRUG LABEL: Dermatool Fungal Nail Treatment
NDC: 84728-510 | Form: LIQUID
Manufacturer: Papalo Group LLC
Category: otc | Type: HUMAN OTC DRUG LABEL
Date: 20250131

ACTIVE INGREDIENTS: TOLNAFTATE 1 g/100 mL
INACTIVE INGREDIENTS: HYDROGENATED POLYBUTENE (1300 MW); ALMOND OIL; .ALPHA.-TOCOPHEROL ACETATE; ALOE VERA LEAF; BUTYLATED HYDROXYTOLUENE; RICE BRAN OIL; SAFFLOWER OIL; LAVENDER OIL; JOJOBA OIL; MELALEUCA ALTERNIFOLIA (TEA TREE) LEAF OIL

Dermatool Antifungal

ACTIVE INGREDIENT

Tolnaftate 1%

PURPOSE

Antifungal

INDICATIONS AND USAGE

Cures most Athlete's Foot (Tinea Pedis) and Ringworm (Tinea Corporis). Relieves itching, scaling, cracking, burning, redness, sorenes, and irritation and discomfort. Helps prevent most athlete's foot (dermatophytosis) with daily use.

WARNINGS

For external use only.

Do not use on children under 2 years of age unless directed by a doctor.

When using this product avoid contact with eyes.

Stop use and ask a doctor if: irritation occurs, there is no improvement within 4 weeks (for athlete's foot and ringworm).

KEEP OUT OF REACH OF CHILDREN

If swallowed, get medical help or contact a Poison Control Center right away.

DOSAGE AND ADMINISTRATION

For athlete's foot and ringworm: use daily for 4 weeks. Clean the affected area and dry thoroughly. Apply a thin layer of the product over affected area twice daily (morning and night) or as directed by a doctor. Supervise children in the use of this product. This product is not effective for the treatment of ringworm of the scalp or nails. For athlete's foot: pay special attention to spaces between the toes, wear well-fitting, ventilated shoes, and change shoes and socks at least once daily. To prevent athlete's foot, apply once or twice daily (morning and/or night). Apply to skin around the nail and cuticle.

INACTIVE INGREDIENT

Carthamus Tinctorius (Safflower) Seed Oil, Hydrogenated Polyisobutene, Oryza Sativa (Rice) Bran Oil, Sesamum Indicum (Sesame) Seed Oil, Prunus Amygdalus Dulcis (Sweet Almond) Oil, Tocopheryl Acetate, Aloe Barbadensis Leaf Extract, Lavandula Angustifolia (Lavender) Oil, Melaleuca Alternifolia (Tea Tree) Leaf Oil, Simmondsia Chinensis (Jojoba) Seed Oil, BHT.